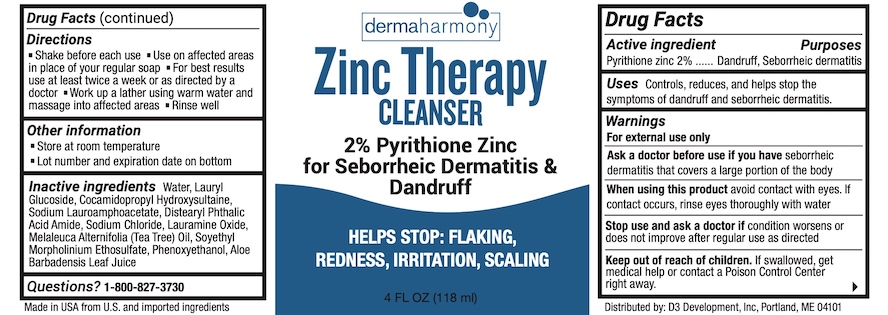 DRUG LABEL: Dermaharmony Zinc Therapy
NDC: 71819-016 | Form: LIQUID
Manufacturer: D3 Development, Inc.
Category: otc | Type: HUMAN OTC DRUG LABEL
Date: 20241220

ACTIVE INGREDIENTS: PYRITHIONE ZINC 2 g/100 mL
INACTIVE INGREDIENTS: SODIUM CHLORIDE; LAURYL GLUCOSIDE; WATER; COCAMIDOPROPYL HYDROXYSULTAINE; SOYETHYL MORPHOLINIUM ETHOSULFATE; DISTEARYL PHTHALAMIC ACID; TEA TREE OIL; LAURAMINE OXIDE; SODIUM LAUROAMPHOACETATE; ALOE VERA LEAF; PHENOXYETHANOL

Zinc Therapy Cleanser

Drug Facts

Active ingredient

Pyrithione zinc 2%

Purposes

Dandruff, Seborrheic dermatitis

Uses

Controls, reduces, and helps stop the symptoms of dandruff and seborrheic dermatitis.

Warnings

For external use only

Ask a doctor before use if you haveseborrheic dermatitis that covers a large portion of the body

WHEN USING

When using this productavoid contact with eyes. If contact occurs, rinse eyes thoroughly with water.

Stop use and ask a doctor ifcondition worsens or does not improve after regular use as directed.

Keep out of reach of children.If swallowed, get medical help or contact a Poison Control Center right away.

Directions

- Shake before each use
- Use on affected areas in place of your regular soap
- For best results use at least twice a week or as directed by a doctor
- Work up a lather using warm water and massage into affected areas
- Rinse well

Other information

- Store at room temperature
- Lot number and expiration date on bottom

Inactive ingredients

Water, Lauryl Glucoside, Cocamidopropyl Hydroxysultaine, Sodium Lauroamphoacetate, Distearyl Phthalic Acid Amide, Sodium Chloride, Lauramine Oxide, Melaleuca Alternifolia (Tea Tree) Oil, Soyethyl Morpholinium Ethosulfate, Phenoxyethanol, Aloe Barbadensis Leaf Juice

Questions?

1-800-827-3730

Distributed by: D3 Development, Inc., Portland, ME 04101

Made in USA from U.S. and imported ingredients

PACKAGE LABEL

dermaharmony

Zinc Therapy CLEANSER

2% Pyrithione Zinc for Seborrheic Dermatitis & Dandruff

HELPS STOP: FLAKING, REDNESS, IRRITATION, SCALING

4 FL OZ (118 ml)